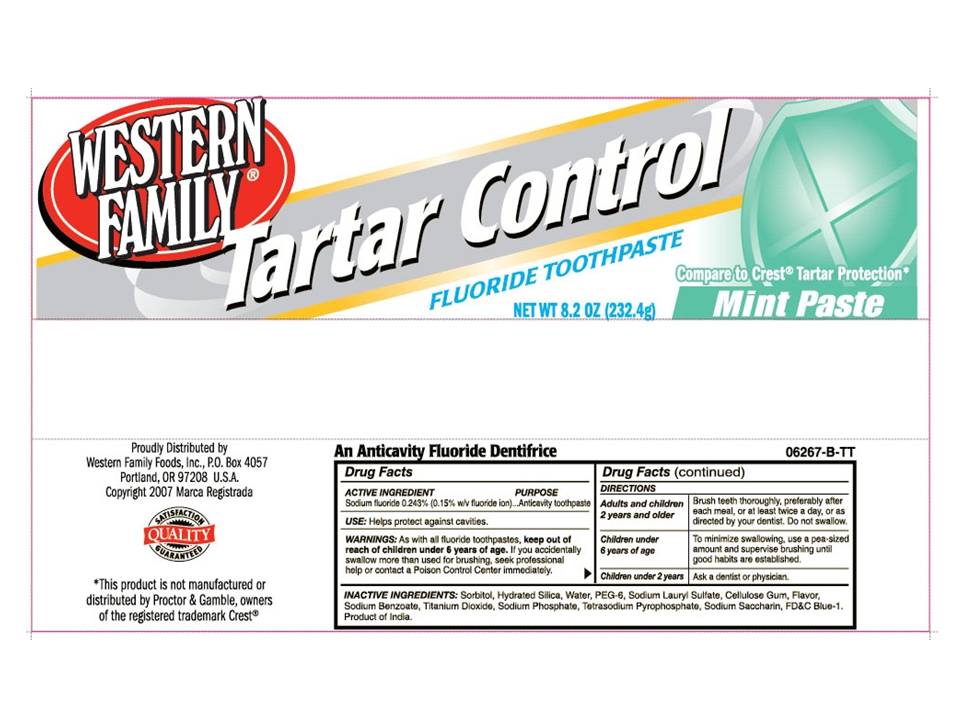 DRUG LABEL: Western Family Tartar Control
NDC: 55312-163 | Form: PASTE, DENTIFRICE
Manufacturer: Western Family Foods, Inc
Category: otc | Type: HUMAN OTC DRUG LABEL
Date: 20110321

ACTIVE INGREDIENTS: Sodium Fluoride 2.43 mg/1 g
INACTIVE INGREDIENTS: SORBITOL; SILICON DIOXIDE; WATER; POLYETHYLENE GLYCOL 300; SODIUM LAURYL SULFATE; CARBOXYMETHYLCELLULOSE SODIUM; SODIUM BENZOATE; TITANIUM DIOXIDE; SODIUM PYROPHOSPHATE; SODIUM PYROPHOSPHATE; SACCHARIN SODIUM; FD&C BLUE NO. 1

Western Family Tartar Control Fluoride Toothpaste

Active Ingredient

Sodium Fluoride 0.243% (0.15% w/v fluoride ion)...Anticavity toothpaste

INDICATIONS AND USAGE

Helps protect against cavities.

WARNINGS

As with all fluoride toothpastes, keep out of reach of children under 6 years of age. If you accidentally swallow more than used for brushing, seek professional help or contact a Poison Control Center immediately.

DOSAGE AND ADMINISTRATION

Adults and children Brush teeth throughly, preferably after
2 years and older each meal, or at least twice a day, or as
directed by your dentist. Do not swallow.

Children under To minimize swallowing, use a pea-sized
6 years of age amount and supervise brushing until
good habits are established.

Children under 2 years Ask a dentist or physician.

Inactive Ingredients:

Sorbitol, Hydrated Silica, Water, PEG-6, Sodium Lauryl Sulfate, Cellulose Gum, Flavor, Sodium Benzoate, Titanium Dioxide, Sodium Phosphate, Tetrasodium Pyrophosphate, Sodium Saccharin, FDC Blue 1